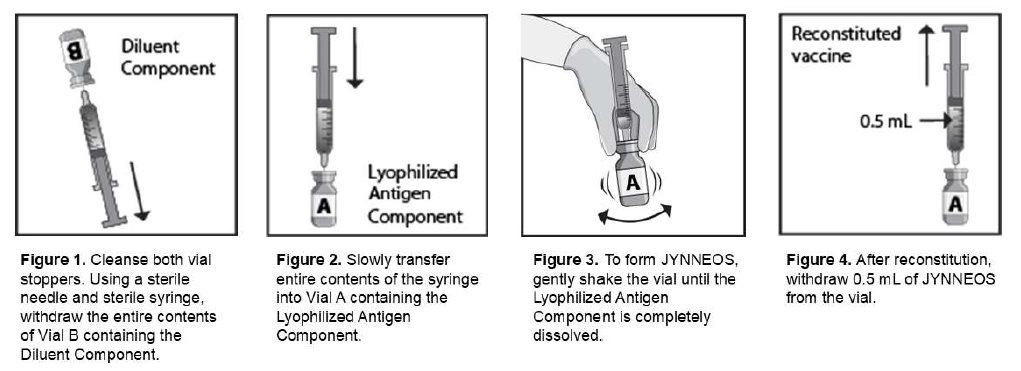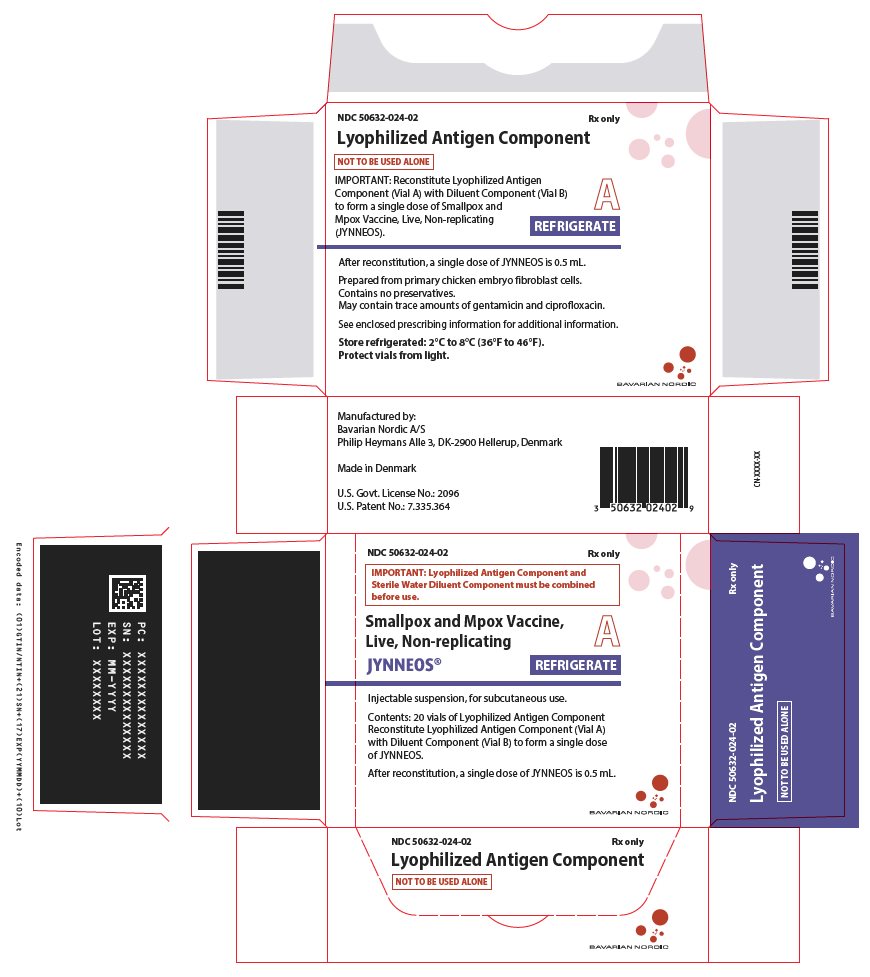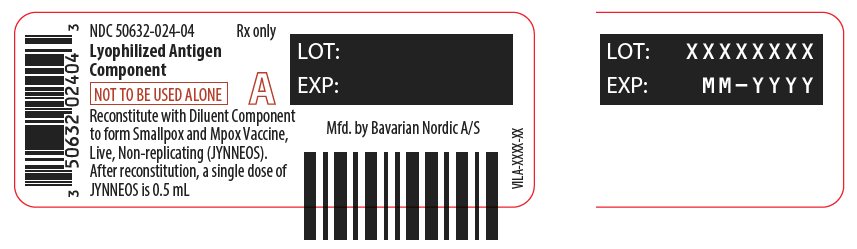 DRUG LABEL: JYNNEOS
NDC: 50632-024 | Form: INJECTION, POWDER, LYOPHILIZED, FOR SUSPENSION
Manufacturer: Bavarian Nordic A/S
Category: other | Type: VACCINE LABEL
Date: 20250331

ACTIVE INGREDIENTS: VACCINIA VIRUS MODIFIED STRAIN ANKARA-BAVARIAN NORDIC NON-REPLICATING ANTIGEN 50000000 1/0.5 mL
INACTIVE INGREDIENTS: TROMETHAMINE; SODIUM CHLORIDE; DEXTRAN 40; SUCROSE; MONOPOTASSIUM GLUTAMATE; WATER

HIGHLIGHTS OF PRESCRIBING INFORMATION

These highlights do not include all the information needed to use JYNNEOS safely and effectively. See full prescribing information for JYNNEOS.
JYNNEOS (Smallpox and Mpox Vaccine, Live, Non-replicating) injectable suspension, for subcutaneous use
Initial U.S. Approval: 2019

RECENT MAJOR CHANGES

Dosage and Administration (2) 03/2025

1 INDICATIONS AND USAGE

JYNNEOS is a vaccine indicated for prevention of smallpox and mpox disease in adults 18 years of age and older determined to be at high risk for smallpox or monkeypox infection. (1)

2 DOSAGE AND ADMINISTRATION

For subcutaneous use. (2)

JYNNEOS is supplied in two presentations:

One-Vial Presentation:

The one-vial presentation contains JYNNEOS in a single vial with a yellow cap and does not require reconstitution before use. (2.1, 2.2)

Two-Vial Presentation:

The two-vial presentation includes a vial with a yellow cap containing Lyophilized Antigen Component and a vial with a blue cap containing Diluent Component. The Lyophilized Antigen Component must be reconstituted with the Diluent Component to form JYNNEOS prior to administration. (2.1, 2.2)

Administer two doses (0.5 mL each) 4 weeks apart. (2.4)

3 DOSAGE FORMS AND STRENGTHS

Injectable suspension. A single dose is 0.5 mL. (3)

6 ADVERSE REACTIONS

- In smallpox vaccine-naïve healthy adults, the most common (> 10%) solicited injection site reactions were pain (84.9%), redness (60.8%), swelling (51.6%), induration (45.4%), and itching (43.1%); the most common solicited systemic adverse reactions were muscle pain (42.8%), headache (34.8%), fatigue (30.4%), nausea (17.3%) and chills (10.4%). (6.1)
- In healthy adults previously vaccinated with a smallpox vaccine, the most common (> 10%) solicited injection site reactions were redness (80.9%), pain (79.5%), induration (70.4%), swelling (67.2%), and itching (32.0%); the most common solicited systemic adverse reactions were fatigue (33.5%), headache (27.6%), and muscle pain (21.5%). (6.1)
- The frequencies of solicited local and systemic adverse reactions among adults with HIV-infection and adults with atopic dermatitis were generally similar to those observed in healthy adults. (6.1)

To report SUSPECTED ADVERSE REACTIONS, contact Bavarian Nordic at toll-free phone 1-833-365-9596 or VAERS at 1-800-822-7967 or www.vaers.hhs.gov.

FULL PRESCRIBING INFORMATION

1 INDICATIONS AND USAGE

JYNNEOS is a vaccine indicated for prevention of smallpox and mpox disease in adults 18 years of age and older determined to be at high risk for smallpox or monkeypox infection.

2 DOSAGE AND ADMINISTRATION

For subcutaneous use.

2.1 JYNNEOS Presentations

JYNNEOS is supplied in two presentations, a one vial-presentation and a two-vial presentation.

One-Vial Presentation

The one-vial presentation contains JYNNEOS in a single vial with a yellow cap and does not require reconstitution before use.

Two-Vial Presentation

The two-vial presentation includes a vial with a yellow cap containing Lyophilized Antigen Component (Vial A) and a vial with a blue cap containing Diluent Component (Vial B). The Lyophilized Antigen Component must be reconstituted with the Diluent Component to form JYNNEOS prior to administration.

2.2 Preparation

Instructions for JYNNEOS One-Vial Presentation

Allow the vaccine to thaw and reach room temperature before use. Once thawed, the vaccine may be kept at +2°C to +8°C (+36°F to +46°F) for 4 weeks. Protect from light during storage.

Do not refreeze.

Swirl the vial gently before use for at least 30 seconds. Withdraw a dose of 0.5 mL into a sterile syringe for injection.

Reconstitution Instructions for JYNNEOS Two-Vial Presentation

Reconstitute the Lyophilized Antigen Component (Vial A, yellow cap) with Diluent Component (Vial B, blue cap) to form JYNNEOS, as described in Figure 1 through Figure 4.

After reconstitution, the vaccine may be stored at +2°C to +8°C (+36°F to +46°F) for 12 hours. Protect from light during storage.

2.3 Administration

JYNNEOS is a milky, light yellow to pale white colored suspension. Parenteral drug products should be inspected visually for particulate matter and discoloration prior to administration, whenever solution and container permit. If either of these conditions exist, the vaccine should not be administered.

Administer each 0.5 mL dose of JYNNEOS subcutaneously.

2.4 Dose and Schedule

Administer two doses (0.5 mL each) of JYNNEOS 4 weeks apart.

3 DOSAGE FORMS AND STRENGTHS

JYNNEOS is an injectable suspension. A single dose is 0.5 mL.

5 WARNINGS AND PRECAUTIONS

5.1 Severe Allergic Reactions

Appropriate medical treatment must be available to manage possible anaphylactic reactions following administration of JYNNEOS.

Persons who experienced a severe allergic reaction following a previous dose of JYNNEOS or following exposure to any component of JYNNEOS may be at increased risk for severe allergic reactions after JYNNEOS. The risk for a severe allergic reaction should be weighed against the risk for disease due to smallpox or mpox.

5.2 Syncope

Syncope (fainting) has been reported following vaccination with JYNNEOS. Procedures should be in place to avoid injury from fainting.

5.3 Altered Immunocompetence

Immunocompromised persons, including those receiving immunosuppressive therapy, may have a diminished immune response to JYNNEOS.

5.4 Limitations of Vaccine Effectiveness

Vaccination with JYNNEOS may not protect all recipients.

6 ADVERSE REACTIONS

6.1 Clinical Trials Experience

Because clinical trials are conducted under widely varying conditions, adverse reaction rates observed in the clinical trials of a vaccine cannot be directly compared with rates in the clinical trials of another vaccine, and may not reflect the rates observed in practice. There is the possibility that broad use of JYNNEOS could reveal adverse reactions not observed in clinical trials.

Safety data accrued with the one-vial presentation is relevant to the two-vial presentation because each contains the same live, attenuated, non-replicating orthopoxvirus and is manufactured using a similar process.

The overall clinical trial program included 23 studies (14 studies with the one-vial presentation, 7 studies with the two-vial presentation, and 2 studies with both one-vial and two-vial presentations) and a total of 8,988 participants 18 through 80 years of age who received at least 1 dose of JYNNEOS (8,222 smallpox vaccine-naïve and 766 smallpox vaccine-experienced participants). Of the 8,988 participants, 6,459 participants received the one-vial presentation and 2,529 participants received the two-vial presentation.

Solicited Adverse Reactions

Solicited Adverse Reactions in Smallpox Vaccine-Naïve Individuals:

The safety of JYNNEOS one-vial presentation in smallpox vaccine-naïve participants was evaluated in Study 1 [1], a randomized, double-blind, placebo-controlled study conducted in the US in which vaccinia-naïve adults ages 18 to 40 years received either two doses of JYNNEOS (N=3,003), or two injections of Tris-Buffered Saline (placebo, N=1,002) four weeks apart.

In the total study population, the mean age was 28 years; 47.9% of the participants were men; 77.4% were white/Caucasian, 17.8% black/African American, 1.9% Asian, 0.5% American Indian/Alaska Native, 0.4% Native Hawaiian/Other Pacific, 1.9% other racial groups; and 11.4% of participants were of Hispanic/Latino ethnicity. The demographic distribution was similar in the JYNNEOS and placebo groups.

In Study 1, participants were monitored for local and systemic adverse reactions using diary cards for an 8-day period starting on the day of each vaccination. The frequencies of solicited local and systemic adverse reactions following any dose of JYNNEOS are presented in Table 1.

Table 1: Percentages of Participants with Solicited Local Injection Site Reactions and Systemic Adverse Reactions within 8 Days of Administration of Any Dose of JYNNEOS in Adults 18 to 40 Years of Age, Study 1x
Reaction | JYNNEOS N=2943 % | Placebo N=980 %
Local (Injection site) | -- | --
Pain | 84.9 | 19.1
Pain, Grade 3a | 7.4 | 1.0
Redness | 60.8 | 17.7
Redness ≥ 100 mm | 1.5 | 0.0
Swelling | 51.6 | 5.6
Swelling ≥ 100 mm | 0.8 | 0.0
Induration | 45.4 | 4.6
Induration ≥ 100 mm | 0.3 | 0.0
Itching | 43.1 | 11.7
Itching, Grade 3b | 1.6 | 0.2
Systemic | -- | --
Muscle Pain | 42.8 | 17.6
Muscle Pain, Grade 3b | 2.6 | 0.7
Headache | 34.8 | 25.6
Headache, Grade 3b | 2.4 | 2.1
Fatigue | 30.4 | 20.5
Fatigue, Grade 3b | 3.0 | 1.3
Nausea | 17.3 | 13.1
Nausea, Grade 3b | 1.5 | 1.2
Chills | 10.4 | 5.8
Chills, Grade 3b | 1.0 | 0.3
Feverc | 1.7 | 0.9
Fever, Grade ≥ 3c | 0.2 | 0.0
x NCT01144637
a Grade 3 pain defined as spontaneously painful
b Grade 3 itching, muscle pain, headache, fatigue, nausea and chills defined as preventing routine daily activities
c Fever defined as oral temperature ≥ 100.4°F (≥ 38°C), Grade ≥ 3 fever defined as ≥ 102.2°F (≥ 39.0°C)
N: number of participants in the specified treatment group

In Study 1, the majority of solicited local and systemic adverse reactions reported with JYNNEOS had a median duration of 1 to 6 days. In general, there were similar proportions of participants reporting solicited local or systemic reactions of any severity after Dose 2 of JYNNEOS compared with Dose 1, with the exception of injection site pain, which was more commonly reported following Dose 1 (79.3%) than Dose 2 (69.9%).

The two presentations of JYNNEOS (one-vial and two-vial) were compared in Study 2 [2], a randomized, double-blind, multicenter study conducted in the US in which vaccinia-naïve adults ages 18 to 55 years received two doses of either two-vial presentation (N=325) or one-vial presentation (N=327) JYNNEOS four weeks apart.

The mean age was approximately 28 years for both study groups; 46.5% of the participants were men; 74.7% were White/Caucasian, 22.3% Black/African American, 0.8% Oriental/Asian, 0.2% American Indian/Alaska Native, 0.3% Native Hawaiian/ Pacific Islander, 1.5% multiple racial groups, and 0.3% other racial groups; and 29.2% of participants were of Hispanic/Latino ethnicity. The demographic distribution was similar in the two JYNNEOS treatment groups.

In Study 2, participants were monitored for local and systemic adverse reactions for an 8-day period starting on the day of each vaccination. The frequencies of solicited local and systemic adverse reactions following any dose of JYNNEOS are presented in Table 2.

Table 2: Percentages of Participants with Solicited Local Injection Site Reactions and Systemic Adverse Reactions, Within 7 Days of Administration of Any dose of JYNNEOS in Adults 18 through 40 Years of Age (Full Analysis Set), Study 2x
Reaction | JYNNEOS One-vial; Presentation; N=322; % | JYNNEOS Two-vial; Presentation; N=321; %
Any Local (Injection site) | 93.2 | 94.1
Local (Injection site) ≥ Grade 3 | 13.0 | 24.0
Pain | 85.1 | 90.3
Pain, Grade 3a | 6.8 | 10.9
Redness | 76.7 | 79.4
Redness ≥ 100 mm | 5.0 | 14.6
Swelling | 65.2 | 69.5
Swelling≥ 100 mm | 3.1 | 7.2
Induration | 65.5 | 66.4
Induration≥ 100 mm | 1.6 | 1.9
Itching | 55.0 | 58.9
Itching, Grade 3b | 2.2 | 3.4
Any Systemic | 56.5 | 57.6
Systemic ≥ Grade 3 | 5.9 | 5.9
Headache | 38.8 | 34.9
Headache, Grade 3c | 2.5 | 2.2
Fatigue | 35.1 | 31.8
Fatigue, Grade 3c | 4.7 | 2.8
Muscle Pain | 21.1 | 18.4
Muscle Pain, Grade 3c | 0.3 | 1.6
Nausea | 17.7 | 15.9
Nausea, Grade 3c | 1.2 | 0.6
Chills | 11.8 | 10.9
Chills, Grade 3c | 0.6 | 1.6
Feverd | 7.1 | 10.3
Fever, Grade ≥ 3d | 0.9 | 0.6
x NCT01668537
a Grade 3 pain defined as spontaneously painful/prevention of normal activity.
b Grade 3 itching defined as preventing routine daily activities.
c Grade 3 muscle pain, headache, fatigue, nausea and chills defined as severe; preventing routine daily activities
d Fever defined as oral temperature ≥ 100.4°F (≥ 38°C), Grade ≥ 3 fever defined as ≥ 102.2°F (≥ 39.0°C)
N: Number of participants in the specified treatment group

In Study 2, solicited systemic adverse reactions reported with both presentations had a similar median duration of 1 to 3 days. Solicited local adverse reactions reported with both presentations had a similar median duration of 4 to 6 days, except for injection site induration. The median duration of injection site induration was 11 days for the one-vial presentation and 14 days for the two-vial presentation.

Solicited Adverse Reactions in Persons Previously Vaccinated with a Smallpox Vaccine:

Three studies (Study 3, Study 4, and Study 5 [3-5]) conducted in the US and Germany evaluated the safety of JYNNEOS one-vial presentation in 409 persons previously vaccinated with a smallpox vaccine who received one or two doses of JYNNEOS (mean age 39 years, range 20-80 years; 59% women; 98.8% white/Caucasian; 0.7% Asian; 0.5% black/African American). Participants were monitored for local and systemic adverse reactions using diary cards for an 8-day period starting on the day of each vaccination. Across all three studies, solicited local adverse reactions reported following any dose of JYNNEOS were redness (80.9%), pain (79.5%), induration (70.4%), swelling (67.2%), and itching (32.0%) at the injection site; solicited systemic adverse reactions reported following any dose of JYNNEOS were fatigue (33.5%), headache (27.6%), muscle pain (21.5%), nausea (9.8%), chills (0.7%), and fever (0.5%).

Solicited Adverse Reactions in HIV-infected Individuals:

The safety of JYNNEOS one-vial presentation in HIV-infected participants was evaluated in Study 6 [6], an open label trial conducted in the US that included 351 HIV-infected smallpox vaccine-naïve participants, 131 HIV-infected participants who previously received smallpox vaccine, 88 non-HIV-infected smallpox vaccine-naïve participants and 9 non-HIV-infected participants who had previously received a smallpox vaccine. The demographic distribution (race, ethnicity, and sex) of HIV-infected smallpox vaccine-naïve participants and those who had previously received smallpox vaccine were similar and overall were 17.0% women; 45.8% white/Caucasian; 0.4% Asian; 33.2% black/African American; 19.0% Hispanic/Latino ethnicity; the HIV-infected smallpox vaccine-naïve group tended to be younger (mean age 37 years) compared to those who had previously received a smallpox vaccine (mean age 45 years). Participants had CD4 counts ≥ 200 and ≤ 750 cells/μL at study entry.

Solicited local and systemic adverse reactions were reported at similar or lower frequencies in HIV-infected smallpox vaccine-naïve participants as compared to those seen in non-HIV-infected smallpox vaccine-naive participants in this study.

In HIV-infected participants with previous smallpox vaccine exposure, fever and chills were reported in 1.5% and 8.4% of participants respectively. Frequencies of other solicited local and systemic adverse reactions in this population were similar to those reported in Studies 3-5 in non-HIV-infected participants who had previously received smallpox vaccination.

The safety of JYNNEOS two-vial presentation in HIV-infected participants was evaluated in Study 7 [7], an open label trial conducted in the US that included 30 HIV-infected smallpox vaccine-naïve participants, 61 HIV-infected participants who previously received smallpox vaccine, 30 non-HIV-infected smallpox vaccine-naïve participants, and 30 non-HIV-infected participants who had previously received a smallpox vaccine. The demographic distribution (race, ethnicity, and sex) of HIV-infected smallpox vaccine-naïve participants and those who had previously received smallpox vaccine were similar. Overall for HIV-infected participants, 29.7% of participants were women; 58.2% were white/Caucasian; 40.7% black/African American; 1.1% other race; Hispanic/Latino ethnicity was not reported; the HIV-infected smallpox vaccine-naïve group tended to be younger (mean age approximately 31 years) compared to those who had previously received a smallpox vaccine (mean age approximately 43 years). Participants had CD4 counts > 350 cells/μL at study entry.

Solicited local and systemic adverse reactions were reported at similar or lower frequencies in HIV-infected smallpox vaccine-naïve participants as compared to those seen in non-HIV-infected smallpox vaccine-naive participants who received the two-vial presentation in this study with the exception of fatigue (40.7% HIV-infected, 36.7% non-HIV infected).

Study 7 also evaluated the safety of a single dose of JYNNEOS two-vial presentation in 61 HIV-infected participants who previously received a smallpox vaccine and 30 non-HIV-infected participants who previously received a smallpox vaccine. Overall for participants who previously received a smallpox vaccine, the mean age was approximately 44 years, range 35-55 years; 44% women; 63.7% white/Caucasian; 34.1% black/African American; 2.2% other race. Participants were monitored for local and systemic adverse reactions for an 8-day period starting on the day of each vaccination. Solicited local adverse reactions reported among both HIV-infected and non HIV-infected participants previously vaccinated with a smallpox vaccine following a single dose of JYNNEOS two-vial presentation were redness (54.9%), pain (84.6%), induration (38.5%), swelling (45.1%), and itching (18.7%) at the injection site; solicited systemic adverse reactions reported following any dose of JYNNEOS were fatigue (38.5%), headache (37.4%), muscle pain (42.9%), nausea (27.5%), chills (16.5%), and fever (2.2%).

In HIV-infected participants with previous smallpox vaccine exposure who received the two-vial presentation, solicited local and systemic adverse reactions were reported at similar or lower frequencies compared to those reported in non-HIV-infected participants who previously received smallpox vaccination in this study.

Solicited Adverse Reactions in Individuals with Atopic Dermatitis:

The safety of JYNNEOS one-vial presentation in smallpox vaccine-naïve participants with currently active or a history of atopic dermatitis (AD) was evaluated in a multicenter, open-label clinical study (Study 8 [8]) conducted in the US and Mexico that included 350 participants with AD and 282 participants without AD. In the overall study the mean age of participants was 27 years (range 18-42 years), and participants were 59.0% women, 39.4% white/Caucasian, 10.9% Asian, 9.0% black/African American, 2.2% Other, and 38.4% Hispanic/Latino ethnicity. Demographic distribution was similar between participants with and without AD. In participants with AD, solicited local and systemic adverse reactions were reported at similar frequencies as those in participants without AD in this study, with the exception of redness (61.2% with AD vs. 49.3% without AD), swelling (52.2% with AD vs. 40.8% without AD), chills (15.9% with AD vs. 7.8% without AD) and headache (47.2% with AD vs. 34.8% without AD).

The safety of JYNNEOS two-vial presentation in smallpox vaccine-naïve participants with currently active or a history of atopic dermatitis (AD) was evaluated in an open-label, controlled clinical study (Study 9 [9]) conducted in Germany that included 31 participants with AD and 29 participants without AD. In the overall study, the mean age was approximately 25 years (range 19-34 years), and participants were 48.3% women, 95% white/Caucasian, 3.3% Asian, 1.7% black/African American; Hispanic/Latino ethnicity was not reported. The demographic distribution was similar between participants with AD and participants without AD. In participants with AD, solicited local and systemic adverse reactions were reported at similar frequencies as those in participants without AD in this study.

The following solicited local and systemic adverse reactions were reported at a greater frequency in participants with AD than those without AD in this study: redness (96.8% with AD vs. 89.7% without AD), itching (25.8% with AD vs. 13.8% without AD), fatigue (67.7% with AD vs. 51.7% without AD), headache (54.8% with AD vs. 44.8% without AD), myalgia (29% with AD vs. 24.1% without AD), and nausea (16.1% with AD vs. 10.3% without AD).

Serious Adverse Events

The integrated analyses of serious adverse events (SAEs) pooled safety data across 23 studies, which included a total of 8,222 smallpox vaccine-naïve participants and 766 smallpox vaccine-experienced participants who received at least 1 dose of JYNNEOS and 1,219 smallpox vaccine-naïve participants and 1 smallpox vaccine-experienced participant who received placebo only. SAEs were monitored from the day of the first study vaccination through at least 6 months after the last study vaccination.

Overall, SAEs were reported to occur in 1.5% (136/8,988) of JYNNEOS (one-vial or two-vial presentation) recipients and 1.4% (17/1,220) of placebo recipients. Among the smallpox vaccine-naïve participants, SAEs were reported for 1.3% (78/5,805) of JYNNEOS one-vial presentation recipients, 1.7% (40/2,417) of JYNNEOS two-vial presentation participants, and 1.4% (17/1,219) of placebo recipients. Among the smallpox vaccine-experienced participants enrolled in studies, SAEs were reported for 2.3% (15/654) of JYNNEOS one-vial presentation recipients and 2.7% (3/112) of JYNNEOS two-vial presentation recipients. Across all studies, a causal relationship to JYNNEOS could not be excluded for 5 SAEs, all non-fatal, which included Crohn’s disease, sarcoidosis, extraocular muscle paresis, throat tightness, and hemolytic anemia.

Cardiac Adverse Events of Special Interest

Evaluation of cardiac adverse events of special interest (AESIs) included any cardiac signs or symptoms, ECG changes determined to be clinically significant, or troponin-I elevated above 2 times the upper limit of normal. In the 23 studies, participants were monitored for cardiac-related signs or symptoms through at least 6 months after the last vaccination.

The numbers of JYNNEOS and placebo recipients, respectively, with troponin-I data were: baseline level (7,505 and 1,203); level two weeks after first dose (6,284 and 1,166); level two weeks after second dose (1,684 and 193); unscheduled visit, including for clinical evaluation of suspected cardiac adverse events (501 and 60).

Overall, cardiac AESIs were reported to occur in 1.3% (112/8,988) of JYNNEOS (one-vial or two-vial presentation) recipients and 0.2% (3/1,220) of placebo recipients. The higher proportion of JYNNEOS one-vial presentation recipients who experienced cardiac AESIs was driven by 28 cases of asymptomatic post-vaccination elevation of troponin-I in two studies: Study 6, which enrolled 482 HIV-infected participants and 97 healthy participants, and Study 8, which enrolled 350 participants with atopic dermatitis and 282 healthy participants. An additional 127 cases of asymptomatic post-vaccination elevation of troponin-I above the upper limit of normal but not above 2 times the upper limit of normal were documented in JYNNEOS recipients throughout the clinical development program, 124 of which occurred in Study 6 and Study 8. Proportions of participants with troponin-I elevations were similar between healthy and HIV-infected participants in Study 6 and between healthy and atopic dermatitis participants in Study 8. A different troponin assay was used in these two studies compared to the other studies, and these two studies had no placebo controls. The clinical significance of these asymptomatic post-vaccination elevations of troponin-I is unknown.

Among the cardiac AESIs reported, 6 cases (<0.1%) were considered to be causally related to JYNNEOS vaccination and included tachycardia, electrocardiogram T wave inversion, electrocardiogram abnormal, electrocardiogram ST segment elevation, electrocardiogram T wave abnormal, and palpitations.

None of the cardiac AESIs considered causally related to study vaccination were considered serious.

6.2 Postmarketing Experience

The following adverse reactions have been identified during postmarketing use of JYNNEOS. Because these reactions are reported voluntarily from a population of uncertain size, it is not always possible to reliably estimate their frequency or establish a causal relationship to vaccine exposure.

Cardiac Disorders: myocarditis, pericarditis

Immune System Disorders: hypersensitivity reactions, including angioedema, rash, and urticaria

Nervous System Disorders: dizziness, syncope, facial paralysis (Bell’s palsy), acute disseminated encephalomyelitis, myelin oligodendrocyte glycoprotein antibody-associated disease, bilateral optic neuritis

General disorders and administration site conditions: injection site warmth, injection site vesicles

8 USE IN SPECIFIC POPULATIONS

8.1 Pregnancy

Risk Summary

All pregnancies have a risk of birth defect, loss, or other adverse outcomes. In the US general population, the estimated background risk of major birth defects and miscarriage in clinically recognized pregnancies is 2% to 4% and 15% to 20%, respectively. Available human data on JYNNEOS administered to pregnant women are insufficient to inform vaccine-associated risks in pregnancy.

The effect of JYNNEOS on embryo-fetal and post-natal development was evaluated in four developmental toxicity studies conducted in female rats and rabbits. In two studies, rats were administered a single human dose of JYNNEOS (0.5 mL) once prior to mating and on one or two occasions during gestation. In the third study, rats were administered a single human dose of JYNNEOS (0.5 mL) on two occasions during gestation. In the fourth study, rabbits were administered a single human dose of JYNNEOS (0.5 mL) once prior to mating and on two occasions during gestation. These animal studies revealed no evidence of harm to the fetus [see Data].

Data

Animal Data

Developmental toxicity studies were conducted in female rats and rabbits. In one study, female rabbits were administered a single human dose of JYNNEOS (0.5 mL) by the subcutaneous route on three occasions: prior to mating, and on gestation days 0 and 14. Three studies were conducted in female rats administered a single human dose of JYNNEOS (0.5 mL) by the subcutaneous route on two or three occasions: prior to mating, and on gestation days 0 and 14; or prior to mating, and on gestation day 0; or on gestation days 0 and 6. No vaccine-related fetal malformations or variations and adverse effects on female fertility or pre-weaning development were reported in these studies.

8.2 Lactation

Risk Summary

It is not known whether JYNNEOS is excreted in human milk. Data are not available to assess the effects of JYNNEOS in the breastfed infant or on milk production/excretion.

The development and health benefits of breastfeeding should be considered along with the mother’s clinical need for JYNNEOS and any potential adverse effects on the breastfed child from JYNNEOS or from the underlying maternal condition. For preventive vaccines, the underlying condition is susceptibility to disease prevented by the vaccine.

8.4 Pediatric Use

Safety and effectiveness of JYNNEOS have not been established in individuals less than 18 years of age.

8.5 Geriatric Use

Forty-two smallpox vaccine-experienced adults 65 to 80 years of age received at least one dose of JYNNEOS (Study 5).

Clinical studies of JYNNEOS did not include sufficient numbers of individuals aged 65 and over to determine whether they respond differently from younger individuals.

11 DESCRIPTION

JYNNEOS (Smallpox and Mpox Vaccine, Live, Non-replicating) is a sterile injectable suspension administered subcutaneously.

JYNNEOS is a live vaccine produced from the strain Modified Vaccinia Ankara-Bavarian Nordic (MVA-BN), an attenuated, non-replicating orthopoxvirus. MVA-BN is grown in primary Chicken Embryo Fibroblast (CEF) cells suspended in a serum-free medium containing no material of direct animal origin, harvested from the CEF cells, purified and concentrated by several Tangential Flow Filtration (TFF) steps including benzonase digestion.

Each 0.5 mL dose of JYNNEOS is formulated to contain 0.5 x 10^8 to 3.95 x 10^8 infectious units of MVA-BN live virus. Each 0.5 mL dose contains 0.61 mg of Tris (tromethamine), 4.09 mg sodium chloride, and may contain residual amounts of host-cell DNA (≤20 mcg), protein (≤500 mcg), benzonase (≤0.0025 mcg), gentamicin (≤0.400 mcg), and ciprofloxacin (≤0.005 mcg). In addition, JYNNEOS vaccine reconstituted with Diluent Component (Water for Injection) contains 9.45 mg dextran 40, 22.5 mg sucrose, and 0.054 mg potassium L-glutamate monohydrate as stabilizers. After preparation [see Dosage and Administration (2.2)], JYNNEOS is a milky, light yellow to pale white colored suspension.

JYNNEOS is formulated without preservatives. The vial stoppers are not made with natural rubber latex.

12 CLINICAL PHARMACOLOGY

12.1 Mechanism of Action

JYNNEOS is an attenuated, live, non-replicating smallpox and mpox vaccine that elicits humoral and cellular immune responses to orthopoxviruses. Vaccinia neutralizing antibody responses in humans were evaluated to establish the effectiveness of JYNNEOS for prevention of smallpox and mpox.

13 NONCLINICAL TOXICOLOGY

13.1 Carcinogenesis, Mutagenesis, Impairment of Fertility

JYNNEOS has not been evaluated for carcinogenic or mutagenic potential, or for impairment of male fertility in animals. Developmental toxicity studies conducted in rats and rabbits vaccinated with JYNNEOS revealed no evidence of impaired female fertility [see Use in Specific Populations (8.1)].

13.2 Animal Toxicology and/or Pharmacology

The efficacy of JYNNEOS to protect cynomolgus macaques (Macaca fascicularis) against a monkeypox virus (MPXV) challenge was evaluated in several studies. Animals were administered Tris-Buffered Saline (placebo) or JYNNEOS (1 x 10^8 TCID50) subcutaneously on day 0 and day 28. On day 63, animals were challenged with MPXV delivered by aerosol (3 x 10^5 pfu), intravenous (5 x 10^7 pfu) or intratracheal (5 x 10^6 pfu) route. Across all studies, 80-100% of JYNNEOS-vaccinated animals survived compared to 0-40% of control animals.

14 CLINICAL STUDIES

14.1 Vaccine Effectiveness

Vaccine effectiveness against smallpox was inferred by comparing the immunogenicity of JYNNEOS to a licensed smallpox vaccine (ACAM2000) based on a Plaque Reduction Neutralization Test (PRNT) using the Western Reserve strain of vaccinia virus and was supported by efficacy data from animal challenge studies. [see Nonclinical Toxicology (13.2)]

Vaccine effectiveness against mpox was inferred from the immunogenicity of JYNNEOS in a clinical study and from efficacy data from animal challenge studies.
[see Nonclinical Toxicology (13.2)]

14.2 Immunogenicity

Study 10 [10] (N=433) was a randomized, open-label study conducted at US military facilities in South Korea to compare the immunogenicity of JYNNEOS to ACAM2000 in healthy smallpox vaccine-naïve adults 18 through 42 years of age. Participants were randomized to receive either two doses of JYNNEOS (N=220) administered 28 days apart or one dose of ACAM2000 (N=213). In the total study population, the mean age was 24 years and 23 years in participants receiving JYNNEOS and ACAM2000, respectively; 82.3% and 86.4% of the participants were men; 57.3% and 63.8% were white/Caucasian, 21.8% and 18.8% black/African American, 6.4% and 5.6% Asian, 3.6% and 2.8% American Indian/Alaska Native, 2.3% and 1.4% Native Hawaiian/Other Pacific, 8.6% and 7.5% other racial groups, and 24.5% and 18.8% of Hispanic/Latino ethnicity (JYNNEOS and ACAM2000, respectively).

The primary immunogenicity endpoint was geometric mean titer (GMT) of vaccinia neutralizing antibodies assessed by PRNT at “peak visits” defined as two weeks after the second dose of JYNNEOS and four weeks after the single dose of ACAM2000. Analyses of antibody responses were performed in the per-protocol immunogenicity (PPI) population, consisting of participants who received all vaccinations and completed all visits up until two weeks after the second dose of JYNNEOS without major protocol violations pertaining to immunogenicity assessments. Table 3 presents the pre-vaccination and “peak visit” PRNT GMTs from Study 10.

Table 3: Comparison of Vaccinia-Neutralizing Antibody Responses Following Vaccination with JYNNEOS or ACAM2000 in Healthy Smallpox Vaccine-Naïve Adults 18 through 42 Years of Age, Study 10x, Per Protocol Set for Immunogenicityy
Time Point | JYNNEOSa (N=185) GMTb [95% CI] | ACAM2000a (N=186) GMTb [95% CI]
Pre-Vaccination | 10.1 [9.9, 10.2] | 10.0 [10.0, 10.0]
Post-Vaccination “Peak Visit”y | 152.8c [133.3, 175.0] | 84.4c [73.4, 97.0]
x NCT01913353
y Per Protocol Set for Immunogenicity included participants who received all vaccinations, completed all visits up until the specified “peak visits” (two weeks after the second dose of JYNNEOS or 4 weeks after the single dose of ACAM2000) without major protocol violations pertaining to immunogenicity assessments.
a JYNNEOS was administered as a series of two doses given 28 days apart, and ACAM2000 was administered as a single dose.
b GMT of vaccinia-neutralizing antibody titers assessed by plaque reduction neutralization test (PRNT) using the Western Reserve vaccinia strain. Values below the assay lower limit of quantitation (LLOQ) of 20 were imputed to a titer of 10; the proportions of participants with pre-vaccination titers less than the assay lower limit of detection were 98.9% among participants randomized to JYNNEOS and 97.8% among participants randomized to ACAM2000, respectively.
c Non-inferiority of the “peak visit” PRNT GMT for JYNNEOS compared to ACAM2000 was demonstrated as the lower bound of the 1-sided 97.5% CI for the GMT ratio (JYNNEOS/ACAM2000) was > 0.5.
N: Number of participants in the specified treatment group; GMT: Geometric Mean Titer; 95% CI: 95% confidence interval, lower limit and upper limit.

PRNT GMTs were also evaluated at pre-specified time points post-vaccination and prior to two weeks after the second dose of JYNNEOS. The PRNT GMTs at two and four weeks after the first dose of JYNNEOS (prior to the second dose), were 23.4 (95% CI: 20.5, 26.7) and 23.5 (95% CI: 20.6, 26.9), respectively. The PRNT GMT at two weeks after the single dose of ACAM2000 was 23.7 (95% CI: 20.9, 26.8).

Study 2 [2] was a randomized, double-blind, multicenter study conducted in the US to assess non-inferiority of immune responses induced by the two-vial presentation of JYNNEOS compared to immune responses induced by the one-vial presentation of JYNNEOS in healthy smallpox vaccine-naïve adults 18 through 55 years of age [see Adverse Reactions (6.1)]. In the Per Protocol Set (PPS; one-vial: N=297; two-vial: N=306), consisting of participants who received all vaccinations and completed all visits up until two weeks after the second dose of JYNNEOS without major protocol violations, the mean age was 28 years for both study groups; 52.9% of the participants in both study groups were women; 72.7% of the participants administered the one-vial presentation of JYNNEOS and 75.2% of the participants administered the two-vial presentation of JYNNEOS were White/Caucasian, 24.2% and 21.9% were Black/African American, respectively, 1.0% and 0% Oriental/Asian, 0% and 0.3% American Indian/Alaska Native, 0.3% and 0.3% Native Hawaiian/Other Pacific, 1.7% and 1.6% multiple racial groups, 0% and 0.7% other racial groups, and 27.3% and 27.5% of Hispanic/Latino ethnicity, respectively.

The primary immunogenicity endpoint was GMT of anti-vaccinia antibodies assessed by Enzyme-linked Immunosorbent Assay (ELISA), and a secondary immunogenicity endpoint was GMT of vaccinia-specific neutralizing antibodies assessed by PRNT at two weeks after the second dose of JYNNEOS. Analyses of antibody responses were performed on the PPS. Table 4 presents the pre-and post-vaccination ELISA and PRNT GMTs from Study 2.

Table 4: Comparison of Antibody Responses Following Vaccination with One-Vial or Two-Vial Presentations of JYNNEOS in Healthy Smallpox Vaccine-Naïve Adults 18 through 55 Years of Age, Study 2x, Per Protocol Sety
Time Point | ELISA |  | PRNT
Time Point | JYNNEOSa; One-Vial; Presentation; (N=297); GMTb [95% CI] | JYNNEOSa; Two-Vial; Presentation; (N=306); GMTb [95% CI] | JYNNEOSa; One-Vial; Presentation; (N=297); GMTc [95% CI] | JYNNEOSa; Two-Vial; Presentation; (N=306); GMTc [95% CI]
Pre-Vaccination | 50.5 [49.7, 51.2] | 50.3 [49.7, 51.0] | 10.2 [9.9, 10.4] | 10.1 [10.0, 10.3]
Two Weeks Post; Dose 2y | 875.1d [801.3,; 955.7] | 1099.6d [1014.8,; 1191.6] | 82.7 [74.3, 92.1] | 100.5 [90.3, 111.8]
x NCT01668537
y Per Protocol Set included participants who received all vaccinations, completed all visits without major protocol violations.
a JYNNEOS was administered as a series of two doses given 4 weeks apart.
b GMT of anti-vaccinia antibody titers assessed by Enzyme-linked Immunosorbent Assay (ELISA). Values below the assay lower limit of quantitation (LLOQ) of 100 were imputed to a titer of 50; the proportions of participants with prevaccination titers less than the assay lower limit of detection were 98.0% among participants randomized to one-vial JYNNEOS and 97.7% among participants randomized to two-vial JYNNEOS.
c GMT of vaccinia-neutralizing antibody titers assessed by Plaque Reduction Neutralization Test (PRNT). Values below the assay LLOQ of 20 were imputed to a titer of 10; the proportions of participants with pre-vaccination titers less than the assay lower limit of detection were 98.0% among participants randomized to one-vial JYNNEOS and 98.7% among participants randomized to two-vial JYNNEOS.
d Non-inferiority of the ELISA GMT for JYNNEOS was demonstrated as the upper bound of the 2-sided 95% CI for the GMT ratio (one-vial JYNNEOS/two-vial JYNNEOS) was below the margin of 1.5.
N: Number of participants in the specified treatment group; GMT: Geometric Mean Titer; 95% CI: 95% confidence interval, lower limit and upper limit.

15 REFERENCES

1. Study 1: NCT01144637
2. Study 2: NCT01668537
3. Study 3: NCT00316524
4. Study 4: NCT00686582
5. Study 5: NCT00857493
6. Study 6: NCT00316589
7. Study 7: NCT00189904
8. Study 8: NCT00316602
9. Study 9: NCT00189917
10. Study 10: NCT01913353

16 HOW SUPPLIED/STORAGE AND HANDLING

16.1 JYNNEOS One-Vial Presentation

How Supplied

JYNNEOS one-vial presentation is supplied in cartons containing either:

- 10 single-dose vials of JYNNEOS (yellow cap), or
- 20 single-dose vials of JYNNEOS (yellow cap)

Table 5: JYNNEOS One-Vial Presentation
Carton | Carton NDC Number | Vial NDC Number
Carton of 10 vials | 50632-023-02 | 50632-023-04
Carton of 20 vials | 50632-022-02 | 50632-022-04

Storage Conditions

Keep frozen at -25°C to -15°C (-13°F to +5°F).

Store in the original package to protect from light.

Do not re-freeze a vial once it has been thawed.

Once thawed, the vaccine may be kept at +2°C to +8°C (+36°F to +46°F) for 4 weeks.

Do not use the vaccine after the expiration.

16.2 JYNNEOS Two-Vial Presentation

How Supplied

JYNNEOS two-vial presentation is supplied in separate cartons:

- 20 vials of Lyophilized Antigen Component (Vial A, yellow cap)
- 20 vials of Diluent Component (Vial B, blue cap)

To form a single dose of JYNNEOS, reconstitute one vial of Lyophilized Antigen Component (Vial A, yellow cap) with one vial of Diluent Component (Vial B, blue cap).

Table 6: JYNNEOS Two-Vial Presentation
Carton | Carton NDC Number | Vial NDC Number
Carton of 20 vials of Lyophilized; Antigen Component | 50632-024-02 | 50632-024-04
Carton of 20 vials of Diluent; Component | 50632-003-02 | 50632-003-01

Storage Before Reconstitution

- Lyophilized Antigen Component:
Store REFRIGERATED at +2°C to +8°C (+36°F to +46°F).
Store in the original package to protect vial from light.
Do not use the vaccine after the expiration date shown on the vial label.
- Diluent Component:
Store at room temperature (+20°C to +25°C, +68°F to +77°F) or refrigerated (+2°C to +8°C, +36°F to +46°F).

Storage After Reconstitution

After reconstitution, use immediately or store refrigerated at +2°C to +8°C (+36°F to +46°F), away from light, for up to 12 hours. Do not freeze reconstituted vaccine.

17 PATIENT COUNSELING INFORMATION

- Inform vaccine recipient of the potential benefits and risks of vaccination with JYNNEOS.
- Inform vaccine recipient of the importance of completing the two dose vaccination series.
- Advise vaccine recipient to report any adverse events to their healthcare provider or to the Vaccine Adverse Event Reporting System at 1-800-822-7967 and www.vaers.hhs.gov.

Manufactured by:
Bavarian Nordic A/S
Philip Heymans Alle 3
2900 Hellerup
Denmark

PRINCIPAL DISPLAY PANEL – Two-Vial Presentation Antigen Carton Label

NDC 50632-024-02 Rx only

IMPORTANT: Lyophilized Antigen Component and
Sterile Water Diluent Component must be combined
before use.

Smallpox and Mpox Vaccine,
Live, Non-replicating

JYNNEOS®

A

REFRIGERATE

Injectable suspension, for subcutaneous use.

Contents: 20 vials of Lyophilized Antigen Component
Reconstitute Lyophilized Antigen Component (Vial A)
with Diluent Component (Vial B) to form a single dose
of JYNNEOS.

After reconstitution, a single dose of JYNNEOS is 0.5 mL.

BAVARIAN NORDIC

PRINCIPAL DISPLAY PANEL - Two-Vial Presentation Antigen Vial Label

NDC 50632-024-04 Rx only

Lyophilized Antigen
Component

NOT TO BE USED ALONE

A

Reconstitute with Diluent Component
to form Smallpox and Mox Vaccine
Live, Non-replicating (JYNNEOS).
After reconstitution, a single dose of
JYNNEOS is 0.5 mL

LOT:

EXP:

Mfd. by Bavarian Nordic A/S

VILA-XXXX-XX